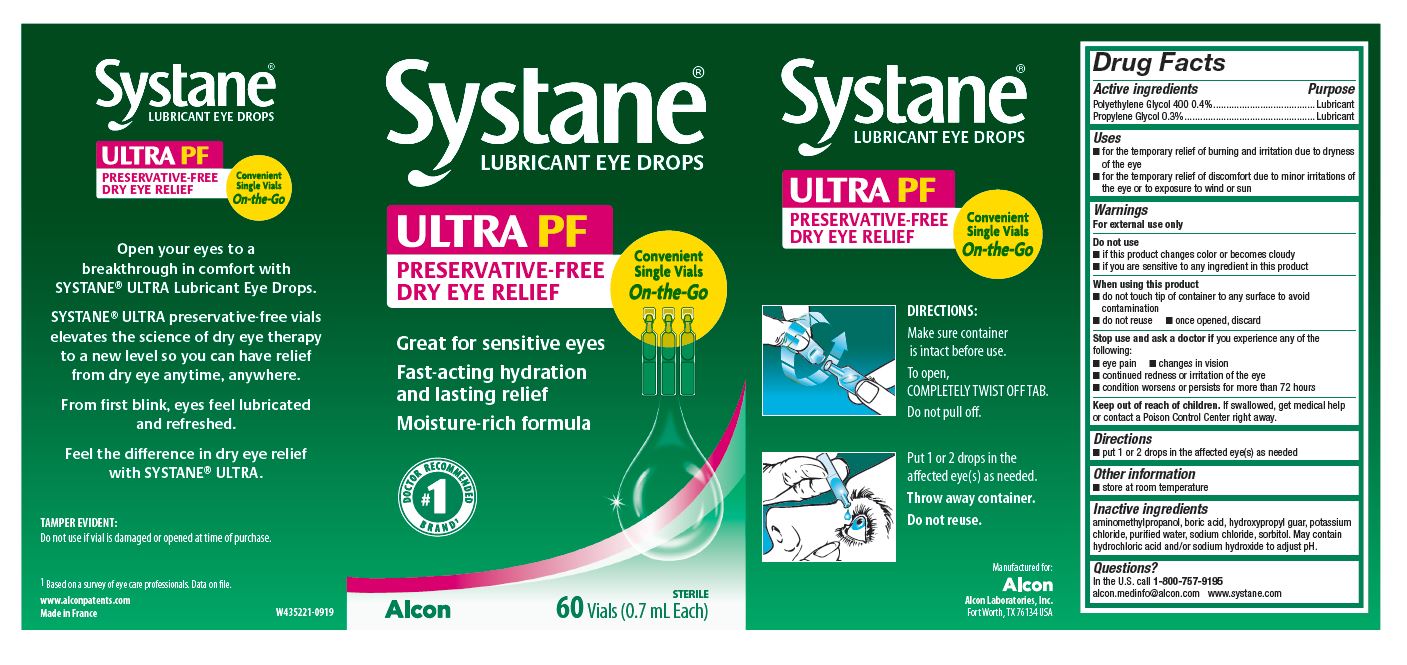 DRUG LABEL: Systane
NDC: 0065-1432 | Form: SOLUTION/ DROPS
Manufacturer: Alcon Laboratories, Inc.
Category: otc | Type: HUMAN OTC DRUG LABEL
Date: 20231215

ACTIVE INGREDIENTS: Polyethylene Glycol 400 4 mg/1 mL; PROPYLENE GLYCOL 3 mg/1 mL
INACTIVE INGREDIENTS: Aminomethylpropanol; BORIC ACID; GUAR GUM; POTASSIUM CHLORIDE; WATER; SODIUM CHLORIDE; SORBITOL; HYDROCHLORIC ACID; SODIUM HYDROXIDE

Drug Facts

Active Ingredients | Purpose
Polyethylene Glycol 400 0.4% | Lubricant
Propylene Glycol 0.3% | Lubricant

Uses

- For the temporary relief of burning and irritation due to dryness of the eye
- for temporary relief of discomfort due to minor irritation of the eye or to exposure to wind or sun

Warnings

For external use only. Do not use

- if this product changes color or becomes cloudy
- if you are sensitive to any ingredient in this product

When using this product

- do not touch tip of container to any surface to avoid contamination
- do not reuse
- once opened, discard

Stop use and ask a doctor if you experience any of the following:

- eye pain
- changes in vision
- Continued redness or irritation of the eye
- Condition worsens or persists for more than 72 hours

Keep out of reach of children.
If swallowed, get medical help or contact a Poison Control Center right away.

Directions

- Put 1 or 2 drops in the affected eye(s) as needed.

Other Information

- Store at room temperature

Inactive Ingredients

Aminomethylpropanol, boric acid, hydroxypropyl guar, potassium chloride, purified water, sodium chloride, sorbitol. May contain hydrochloric acid and/or sodium hydroxide to adjust pH.

Questions?

In the U.S. call 1-800-757-9195
www.systane.com

PRINCIPAL DISPLAY PANEL

Systane®
LUBRICANT EYE DROPS
ULTRA PF
PRESERVATIVE-FREE
DRY EYE RELIEF
Convenient Single Vials On-The-Go
Great for sensitive eyes
Fast-acting hydration
and lasting relief
Moisture-rich formula
#1 Doctor Recommended Brand^1
STERILE
60 Vials 0.7 mL Each
Alcon

SIDE DISPLAY PANEL

Systane®
LUBRICANT EYE DROPS
ULTRA PF
PRESERVATIVE-FREE
DRY EYE RELIEF
Convenient Single Vials On-The-Go
Open your eyes to a
breakthrough in comfort with
SYSTANE® ULTRA Lubricant Eye Drops.
SYSTANE® ULTRA preservative-free vials
elevates the science of dry eye therapy
to a new level so you can have relief
from dry eye anytime, anywhere.
From first blink eyes feel lubricated
and refreshed.
Feel the difference in dry eye relief
with SYSTANE® ULTRA
TAMPER EVIDENT:
Do not use if vial is damaged or opened at time of purchase.
^1Based on a survey of eye care professionals. Data on file.
www.alconpatents.com
Made in France
W435221-0919